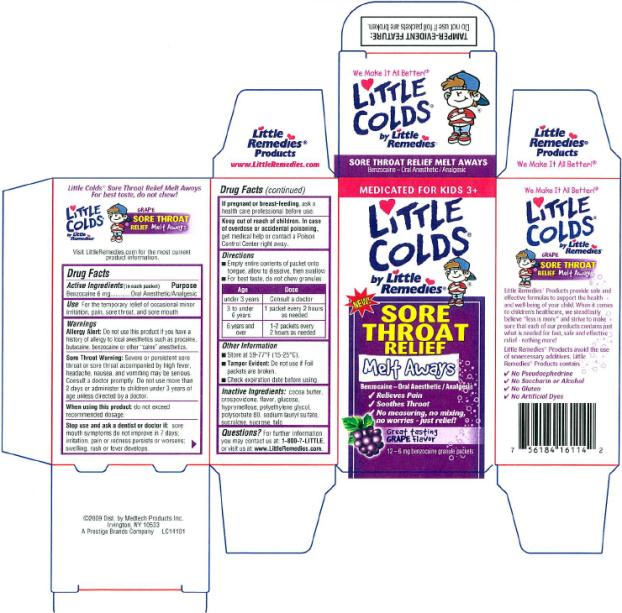 DRUG LABEL: Little Colds Sore Throat Relief Melt Aways
NDC: 63029-102 | Form: GRANULE
Manufacturer: Medtech Products Inc.
Category: otc | Type: HUMAN OTC DRUG LABEL
Date: 20091229

ACTIVE INGREDIENTS: BENZOCAINE 6 mg/1 1

Little Colds Sore Throat Relief Melt Aways

Brand: Little Remedies

Product Name: Little Colds Sore Throat Melt Aways

Size: 12 packets

Country: USA

Artwork Description: IFC

Artwork #: LC14101

Active ingredients

Benzocaine 6 mg (in each packet)

Purpose

Oral Anesthetic/Analgesic

Use

For the temporary relief of occasional minor irritation, pain, sore throat, and sore mouth.

Warnings

Allergy Alert: Do not use this product if you have a history of allergy to local anesthetics such as procaine, butacaine, benzocaine or other “caine” anesthetics.

Sore Throat Warning: Severe or persistent sore throat or sore throat accompanied by high fever, headache, nausea, and vomiting may be serious. Consult a doctor promptly. Do not use more than 2 days or administer to children under (3) years of age unless directed by a doctor.

When using this product:

do not exceed recommended dosage.

Stop use and ask a dentist or doctor if:

sore mouth symptoms do not improve in 7 days; irritation, pain or redness persists or worsens; swelling, rash or fever develops.

If pregnant or breast-feeding

ask a health care professional before use.

Keep out of reach of children.

In case of overdose or accidental poisoning, get medical help or contact a Poison Control Center right away.

Directions

- Empty entire contents of packet onto tongue, allow to dissolve, then swallow
- For best taste, do not chew granules

Age | Dose
under 3 years | Consult a doctor
3 to under 6 years | 1 packet every 2 hours as needed
6 years and over | 1 – 2 packets every 2 hours as needed

Other Information

- Store at 59–77°F (15–25°C).
- Tamper Evident: Do not use if foil packets are broken.
- Check expiration date before using.

Inactive Ingredients

cocoa butter, crospovidone, flavor, glucose, hypromellose, polyethylene glycol, polysorbate 80, sodium lauryl sulfate, sucralose, sucrose, talc

Questions

For further information you may contact us at: 1-800-7-LITTLE, or visit us at www.LittleRemedies.com.

©2009 Dist. by Medtech Products Inc.

Irvington, NY 10533

A Prestige Brands Company

LC14101

PRINCIPAL DISPLAY PANEL

MEDICATED FOR KIDS 3+

LITTLE

Colds®

By Little

Remedies

NEW!

SORE

THROAT

RELIEF

Melt Aways

Benzocaine – Oral Anesthetic / Analgesic

- Relives Pain
- Soothes Throat
- No measuring, no mixing,
  no worries – just relief!

Great tasting

GRAPE flavor

12 - 6 mg Benzocaine granule packets